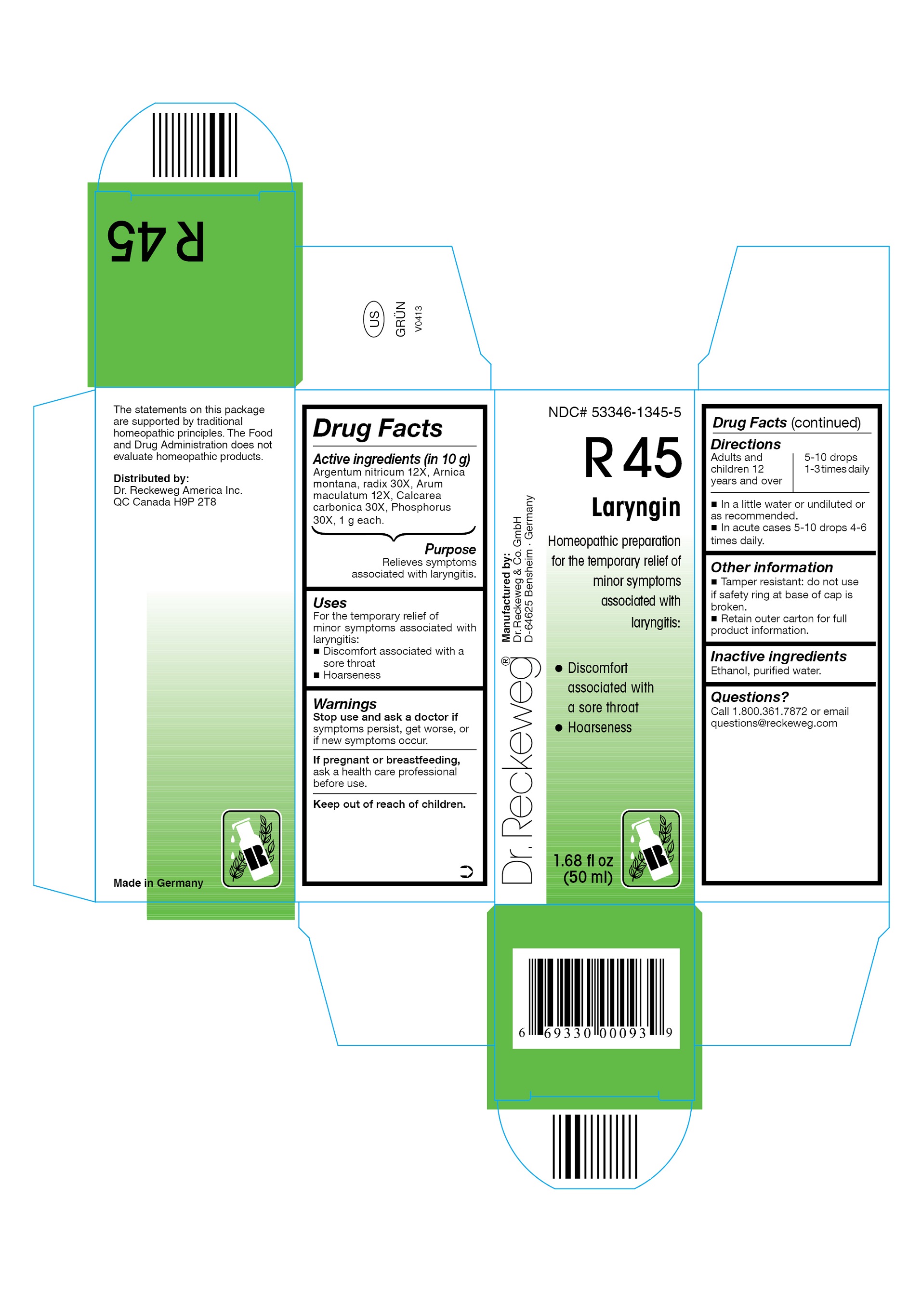 DRUG LABEL: DR. RECKEWEG R45 Laryngin
NDC: 53346-1345 | Form: LIQUID
Manufacturer: PHARMAZEUTISCHE FABRIK DR. RECKEWEG & CO
Category: homeopathic | Type: HUMAN OTC DRUG LABEL
Date: 20130405

ACTIVE INGREDIENTS: SILVER NITRATE 12 [hp_X]/50 mL; ARNICA MONTANA ROOT 30 [hp_X]/50 mL; ARUM MACULATUM ROOT 12 [hp_X]/50 mL; OYSTER SHELL CALCIUM CARBONATE, CRUDE 30 [hp_X]/50 mL; PHOSPHORUS 30 [hp_X]/50 mL
INACTIVE INGREDIENTS: ALCOHOL; WATER

DR. RECKEWEG R45 Laryngin

Active ingredients

Argentum nitricum 12X, Arnica montana, radix 30X, Arum maculatum 12X, Calcarea carbonica 30X, Phosphorus 30X, 1 g each in 10 g.

Purpose

Relieves symptoms associated with laryngitis

Uses

For the temporary relief of minor symptoms associated with laryngitis:

- Discomfort associated with a sore throat
- Hoarseness

Warnings

Stop use and ask a doctor if symptoms persist, get worse, or if new symptoms occur.

PREGNANCY OR BREAST FEEDING

If pregnant or breastfeeding, ask a health care professional before use.

Keep out of reach of children.

Directions
Adults and children ≥ 12 years 5-10 drops 1-3 times daily, acute cases 5-10 drops 4-6 times daily in a little water or undiluted or as recommended.

Other information

- Tamper resistant: do not use if safety ring at base of cap is broken.
- Retain outer carton for full product information.

Inactive ingredients

Ethanol, purified water.

Questions?
Call 1-800-361-7872 or email questions@reckeweg.com

PACKAGE LABEL

NDC# 53346-1345-5

Dr. Reckeweg R45 Laryngin

Homeopathic preparation for the temporary relief of minor symptoms associated with laryngitis:

- Discomfort associated with a sore throat
- Hoarseness

Manufactured by:

Dr. Reckeweg Co. GmbH

D-64625 Bensheim

Germany

1.68 fl oz
(50 ml)